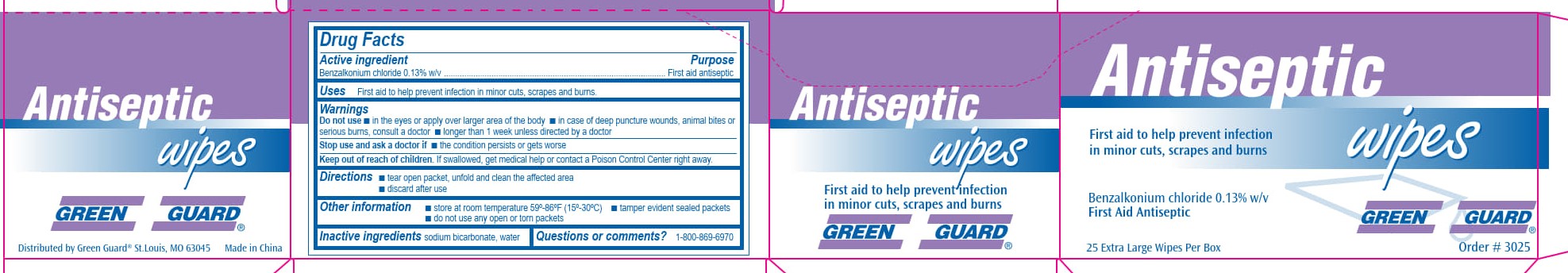 DRUG LABEL: Green Guard Antiseptic Wipes
NDC: 47682-075 | Form: SWAB
Manufacturer: UniFirst First Aid Corporation
Category: otc | Type: HUMAN OTC DRUG LABEL
Date: 20250908

ACTIVE INGREDIENTS: BENZALKONIUM CHLORIDE 1.3 mg/1 mL
INACTIVE INGREDIENTS: WATER; SODIUM BICARBONATE

Green Guard Antiseptic Wipes

Drug Facts

Active Ingredient

Benzalkonium chloride 0.13% w/v

Purpose

First aid antiseptic

Uses

First aid to help prevent infection in minor cuts, scrapes and burns.

Warnings

Do not use

- in the eyes or apply over larger area of the body
- in case of deep puncture wounds, animal bites or serious burns, consult a doctor
- longer than 1 week unless directed by a doctor

Stop use and ask a doctor if

Stop use and ask a doctor it

- the condition persists or gets worse

Keep out of reach of children

If swallowed, get medical help or contact a Poison Control Center right away.

Directions

- tear open packet, unfold and clean the affected area
- discard after use

Other information

- store at room temperature 59º-86ºF (15º-30ºC)
- tamper evident sealed packets
- do not use any open or torn packets

Inactive ingredients

sodium bicarbonate, water

Questions or comments?

1-800-869-6970

Green Guard Antiseptic Wipes

Antiseptic wipes

First aid to help prevent infection

in minor cuts, scrapes and burns

Benzalkonium chlorise 0.13% w/v

First Aid Antiseptic

Green Guard®